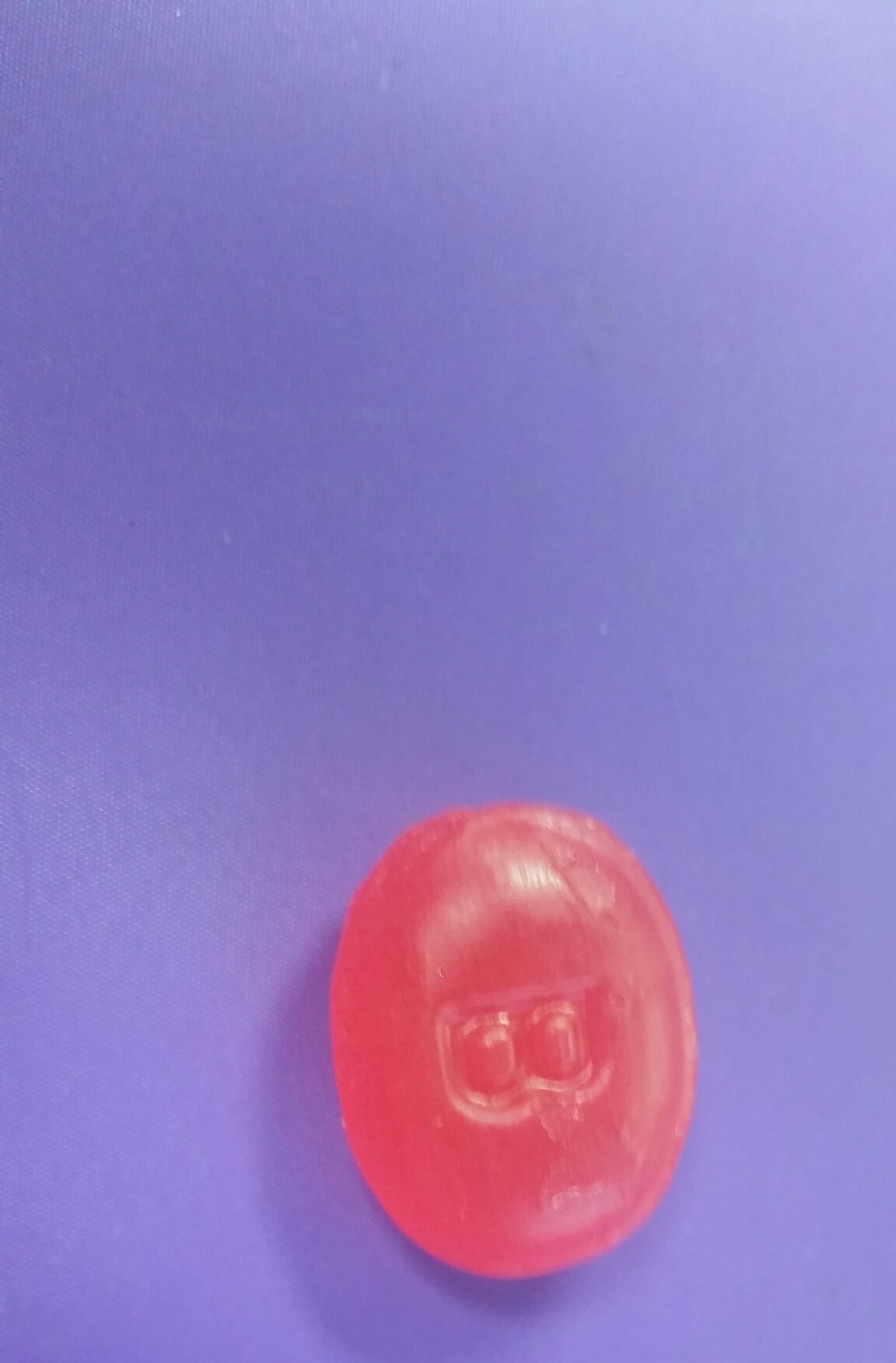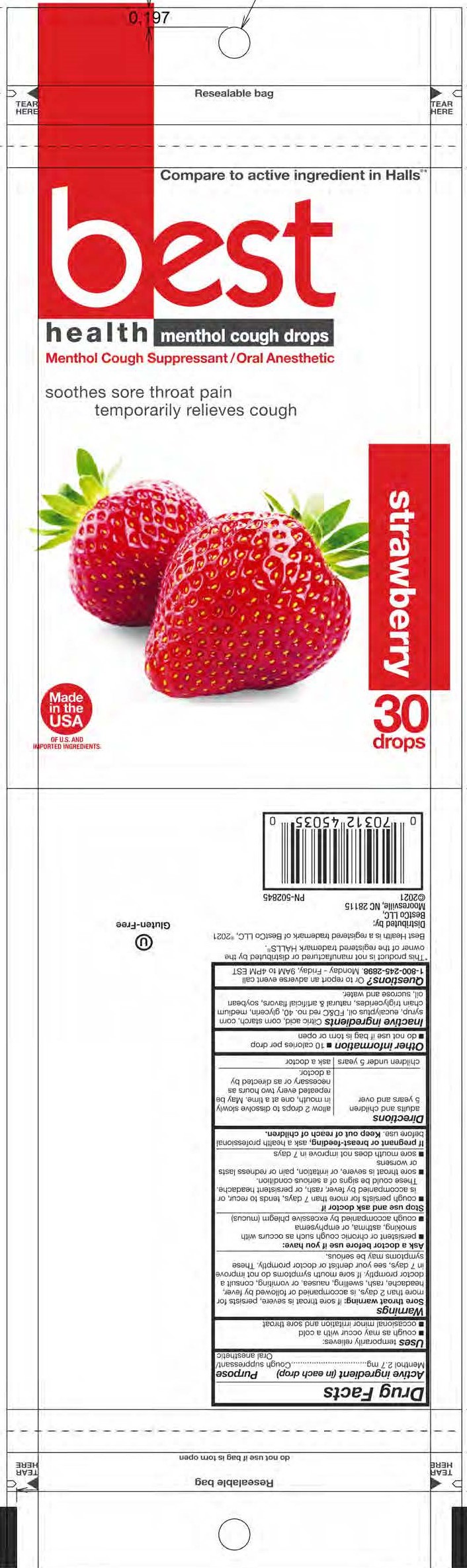 DRUG LABEL: Strawberry Cough Drops
NDC: 52642-020 | Form: LOZENGE
Manufacturer: BestCo Inc.
Category: otc | Type: HUMAN OTC DRUG LABEL
Date: 20251231

ACTIVE INGREDIENTS: MENTHOL 2.7 mg/1 1
INACTIVE INGREDIENTS: CITRIC ACID MONOHYDRATE

Menthol 2.7mg

Active Ingredient (in each drop)

Menthol 2.7mg

Purpose

Cough suppressant / Oral anesthetic

Uses

Temporarily relieves:

- cough as may occur with cold
- occasional minor irritation and sore throat

Warnings

Sore Throat Warning: If sore throat is severe, persists for more than 2 days, is accompanied or followed by fever, headache, rash, swelling, nausea, or vomiting, consult a doctor promptly. If sore mouth symptoms do not improve in 7 days, see your dentist or doctor promptly. These symptoms may be serious.

Ask a doctor before use if you have:

- persistet or chronic cough such as occurs with smoking, asthma, or emphysema.
- cough accompanied by excessive phlegm (mucus)

Stop use and ask doctor if

- cough persists for more than 7 days, tends to recur, or is accompanied by fever, rash, or persistent headache. These could be signs of a serious condition.
- sore throat is severe, or if irritation, pain or redness lasts or worsens.
- sore mouth does not improve in 7 days.

PREGNANCY OR BREAST FEEDING

If pregnant or breast feeding, ask a health professional before use.

Keep out of the reach of chidren.

Directions

Adults and children 5 years and over, allow 2 drops to dissolve in mouth slowly, one at a time. May be repeated every 2 hours a necessary or as directed by a doctor.

Children under 5 years, ask a doctor

Other information:

- 10 calories per drop
- do not use if bag is torn or open

INACTIVE INGREDIENT

Inactive Ingredients: Citric acid, corn starch, corn syrup, eucalyptus oil, FD&C red no. 40, glycerin, medium chain triglycerides, natural and artificial flavors, soybean oil, sucrose and water.

QUESTIONS

Questions? Or to report an adverse event call: 1-800-245-2898 Monday - Friday 9AM to 4PM EST